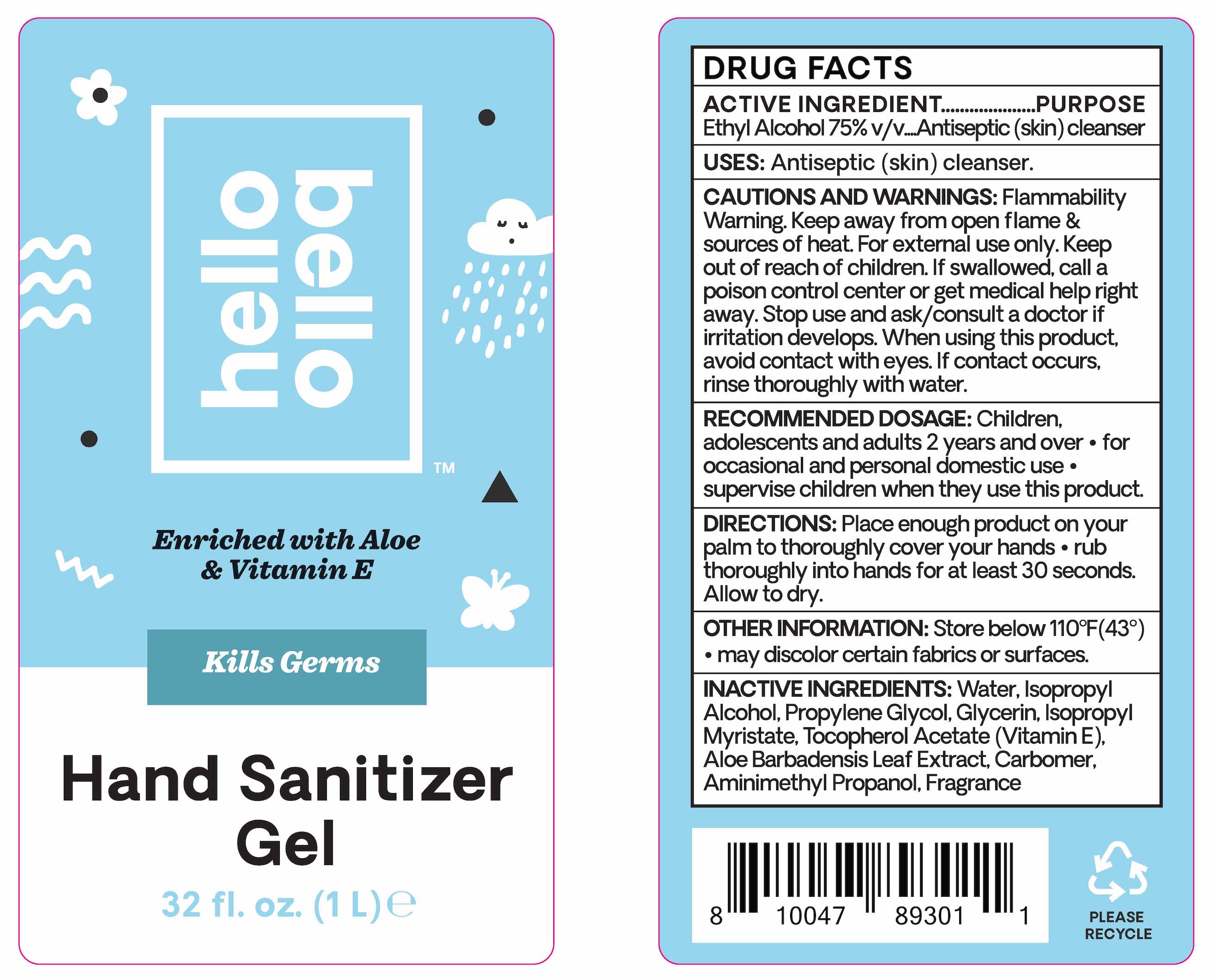 DRUG LABEL: Hand Sanitizer Gel
NDC: 73418-200 | Form: GEL
Manufacturer: Hello Bello
Category: otc | Type: HUMAN OTC DRUG LABEL
Date: 20231030

ACTIVE INGREDIENTS: ALCOHOL 75 mL/1 L
INACTIVE INGREDIENTS: ALOE VERA LEAF; ALPHA-TOCOPHEROL ACETATE; CARBOMER HOMOPOLYMER, UNSPECIFIED TYPE; AMINOMETHYLPROPANOL; ISOPROPYL ALCOHOL; PROPYLENE GLYCOL; ISOPROPYL MYRISTATE; GLYCERIN

Hand Sanitizer Gel Unscented

Active Ingredients

Ethyl Alcohol 75% v/v

Purpose

Antiseptic (skin) cleanser

Uses

Antiseptic (skin) cleanser

Warnings

Flammability warning. Keep away from open flame & sources of heat.

For external use only

Keep out of reach of children

WARNINGS

If swallowed, call a Poison Control Center or get medical help right away.

Stop use and ask/consult a doctor

if irritation develops.

When using this product

, avoid contact with eyes. If contact occurs, rinse thoroughly with water.

Directions

Recommended dosage:

- Children, adolescents and adults 2 years and over
- For occasional and personal domestic use
- Supervise children when they use this product

Place enough product on your palm to thoroughly cover your hands.

Rub thoroughly into hands for at least 30 seconds.

Allow to dry

Other Information

Store below 110F (43C). May discolor certain fabrics or surfaces.

Inactive Ingredients

Water, Isopropyl Alcohol, Propylene Glycol, Glycerin, Isopropyl Myristate, Tocopheryl Acetate (Vitamin E), Aloe Barbadensis Leaf Extract, Carbomer, Aminomethyl Propanol, Fragrance